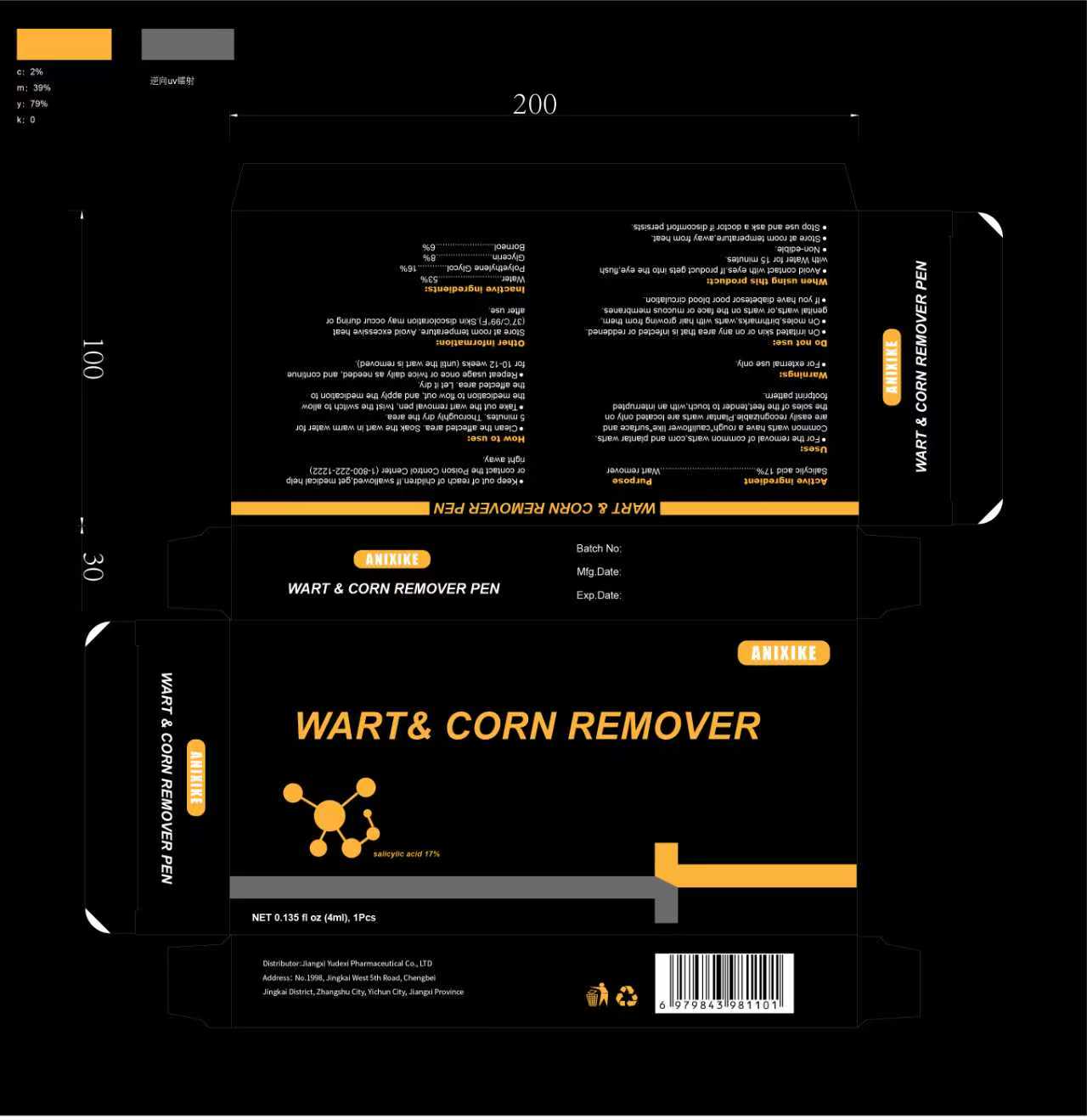 DRUG LABEL: ANIXIKE WART CORN REMOVER PEN
NDC: 85248-141 | Form: LIQUID
Manufacturer: Jiangxi Yudexi Pharmaceutical Co., LTD
Category: otc | Type: HUMAN OTC DRUG LABEL
Date: 20260213

ACTIVE INGREDIENTS: SALICYLIC ACID 17 g/100 mL
INACTIVE INGREDIENTS: BORNEOL; WATER; GLYCERIN; POLYETHYLENE GLYCOL, UNSPECIFIED

85248-141

Active Ingredient

Salicylic acid 17%

Purpose

Wart remover

Use

For the removal of common warts,corn and plantar warts.Common warts have a rough"cauliflower like"surface and are easily recognizable.Plantar warts are located only on the soles of the feet,tender to touch,with an interrupted footprint pattern.

Warnings

For external use only.

Do not use

on irritated skin or on any area that is infected or reddened·on moles, birthmarks, warts with hair growing from them, genital warts or
warts on the face or mucous membranes.If you have diabetes or poor blood circulation.

When Using

Avoid contact with eyes. lf product gets into the eye, flush with Water for 15 minutes.Non-edible. Cap tightly and store at room temperature, away from heat.

Stop Use

Stop use and ask a doctor if discomfort persists.

Ask Doctor

Stop use and ask a doctor if discomfort persists.

Keep Oot Of Reach Of Children

If swallowed, get medical help or contact the Poison Control Center (1-800-222-1222) right away.

Directions

Clean the affected area. Soak the wart in warm water for
5 minutes. Thoroughly dry the area.Take out the wart removal pen, twist the switch to allowthe medication to flow out, and apply the medication to
the affected area. Let it dry.Repeat usage once or twice daily as needed, and continuefor 10-12 weeks (until the wart is removed).

Other information

Store at room temperature.Avoid excessive heat (37°C/ 99°F).Skin discoloration may occur during or after use.

Inactive ingredients

Water，Polyethylene Glycol，Glycerin，Borneol.